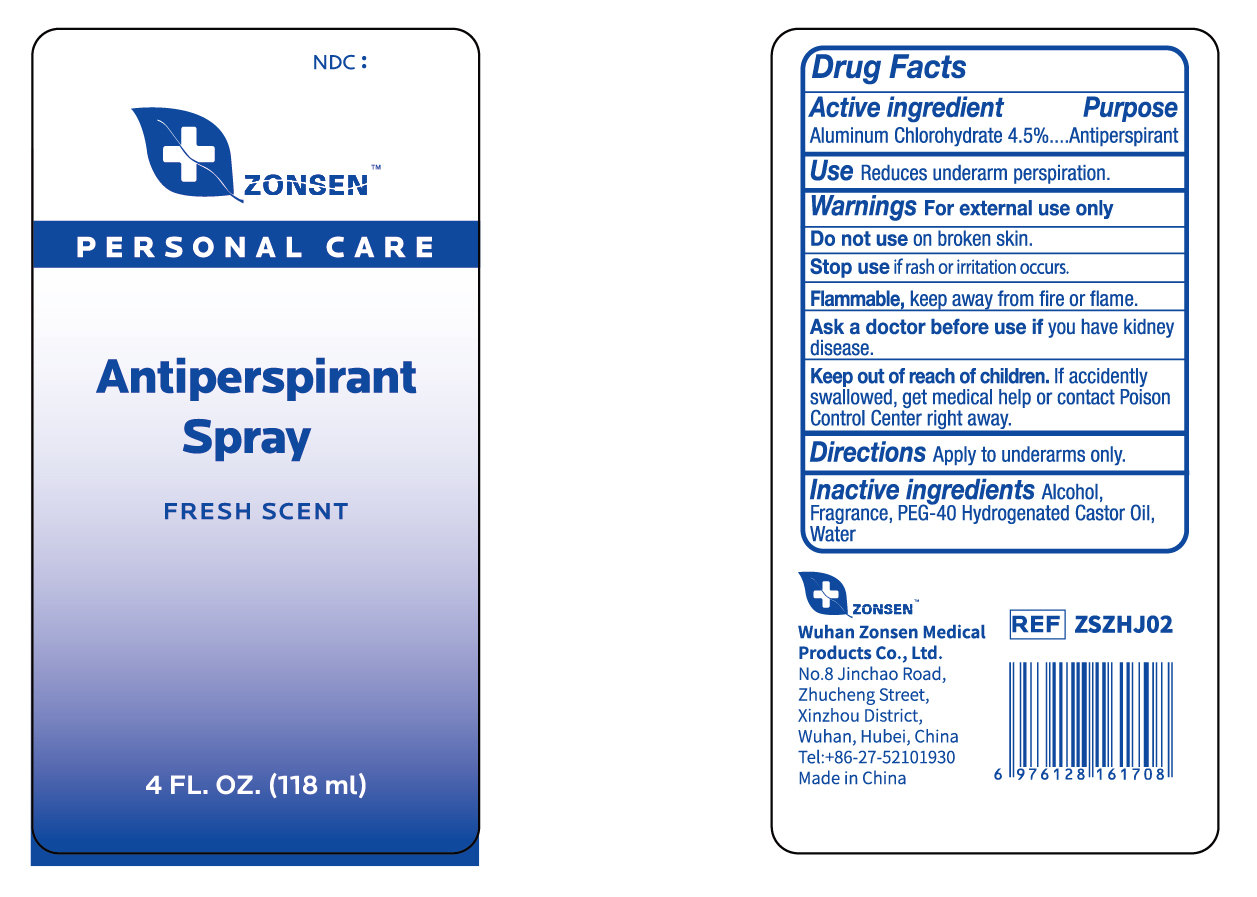 DRUG LABEL: ZONSEN Antiperspirant
NDC: 72932-011 | Form: LIQUID
Manufacturer: Wuhan Zonsen Medical Products Co., Ltd.
Category: otc | Type: HUMAN OTC DRUG LABEL
Date: 20240821

ACTIVE INGREDIENTS: ALUMINUM CHLOROHYDRATE 45 mg/1 mL
INACTIVE INGREDIENTS: WATER; ALCOHOL 95%; POLYOXYL 40 HYDROGENATED CASTOR OIL

ACTIVE INGREDIENT

Aluminum Chlorohydrate 4.5%

PURPOSE

Antiperspirant

Use

Reduces underarm perspiration.

WARNINGS

For external use only.

DO NOT USE

on broken skin.

STOP USE

if rash or irritation occurs.

FLAMMABLE

Keep away from fire or flame.

ASK DOCTOR BEFORE USE

if you have kidney disease.

KEEP OUT OF REACH OF CHILDREN

If accidently swallowed, get medical help or contact Poison Control Center right away

DIRECTIONS

Apply to underarms only.

INACTIVE INGREDIENT

Water, Alcohol, PEG-40 Hydrogenated Castor Oil, Fragrance

DOSAGE & ADMINISTRATION

Use daily for best results.

PACKAGE LABEL

ZONSEN

PERSONAL CARE

Antiperspirant Spray

FRESH SCENT

4FL. OZ. (118ml)